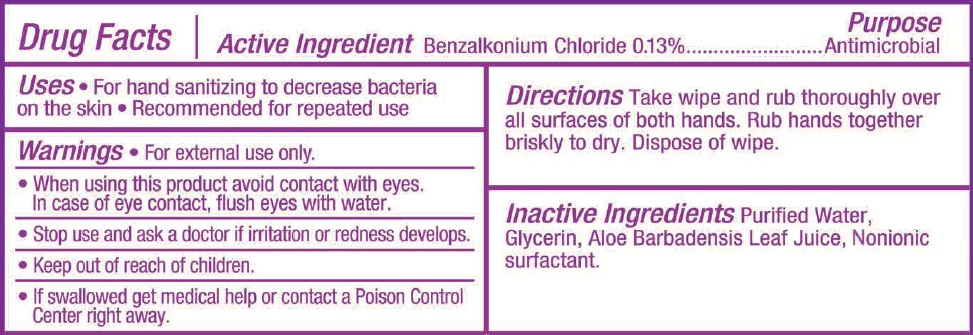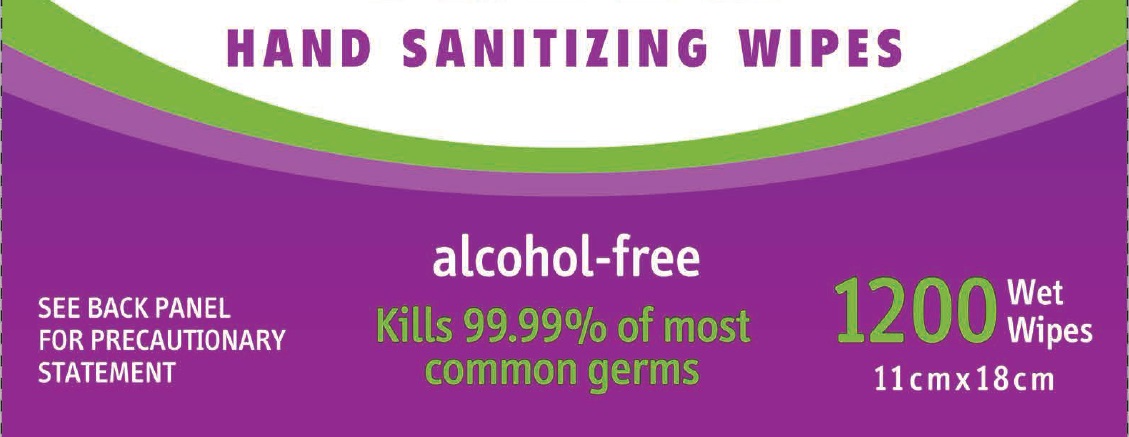 DRUG LABEL: HAND SANITIZER WIPES
NDC: 71766-001 | Form: GEL
Manufacturer: Hangzhou Linkeweier Daily Chemicals Co., Ltd.
Category: otc | Type: HUMAN OTC DRUG LABEL
Date: 20180306

ACTIVE INGREDIENTS: BENZALKONIUM CHLORIDE 0.13 g/100 g
INACTIVE INGREDIENTS: WATER; ALOE VERA LEAF; GLYCERIN

Hand Sanitizing Wipes

Active Ingredient

benzalkonium chloride 0.13%

Purpose

Antimicrobial

Use

for hand sanitizing to decrease bacteria on the skin.

recommended for repeated use

Warning

For external use only

when using this product,avoid contact with eyes,

In case of contact flush eyes with water

Stop use and ask a doctor if irritation or redness develop

if swallowed get medical help or caontact a poison control center reght away.

Keep out of reach of children

Directions

take wipe and rub thoroughly over all surfaces of both hands.rub hands together briskly to dry ,dispose of wipe

INACTIVE INGREDIENT

purified Water,Glycerin,Aloe Barbadensis Leaf Juice,nonionic surfactant